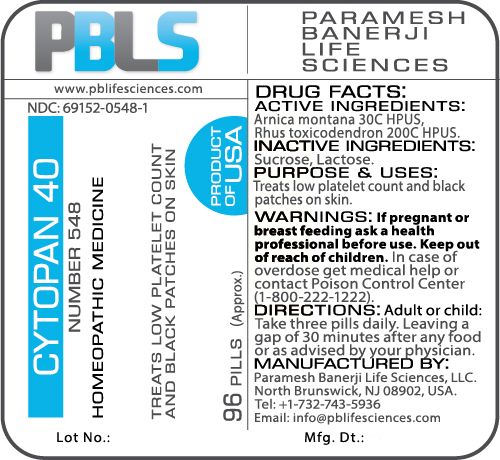 DRUG LABEL: Cytopan 40 (Number 548)
NDC: 69152-0548 | Form: PELLET
Manufacturer: Paramesh Banerji Life Sciences LLC
Category: homeopathic | Type: HUMAN OTC DRUG LABEL
Date: 20180117

ACTIVE INGREDIENTS: ARNICA MONTANA 30 [hp_C]/1 1; TOXICODENDRON PUBESCENS LEAF 200 [hp_C]/1 1
INACTIVE INGREDIENTS: LACTOSE; SUCROSE

DRUG FACTS: Active Ingredients

Arnica montana 30C HPUS, Rhus toxicodendron 200C HPUS

Inactive Ingredients

Sucrose, Lactose

Purpose

Treats low platelet count and black patches on skin

Uses

Treats low platelet count and black patches on skin

Warnings

If pregnant or breast feeding ask a health professional before use.

Keep out of reach of children. In case of overdose, get medical help or contact a Poison Control Center (1-800-222-1222) right away.

Direction

Adult or child: Take three pills daily. Leaving a gap of 30 minutes after any food or as advised by your physician.

Manufactured by

Paramesh Banerji Life Sciences, LLC.

North Brunswick, NJ 08902, USA.

Tel: +1-732-743-5936

Email: info@pblifesciences.com

Principal Display Panel

NDC: 69152-0548-1

Cytopan 40

Number 548

Homeopathic Medicine

Treats low platelet count and black patches of skin

96 Pills (Approx.)

Product of USA